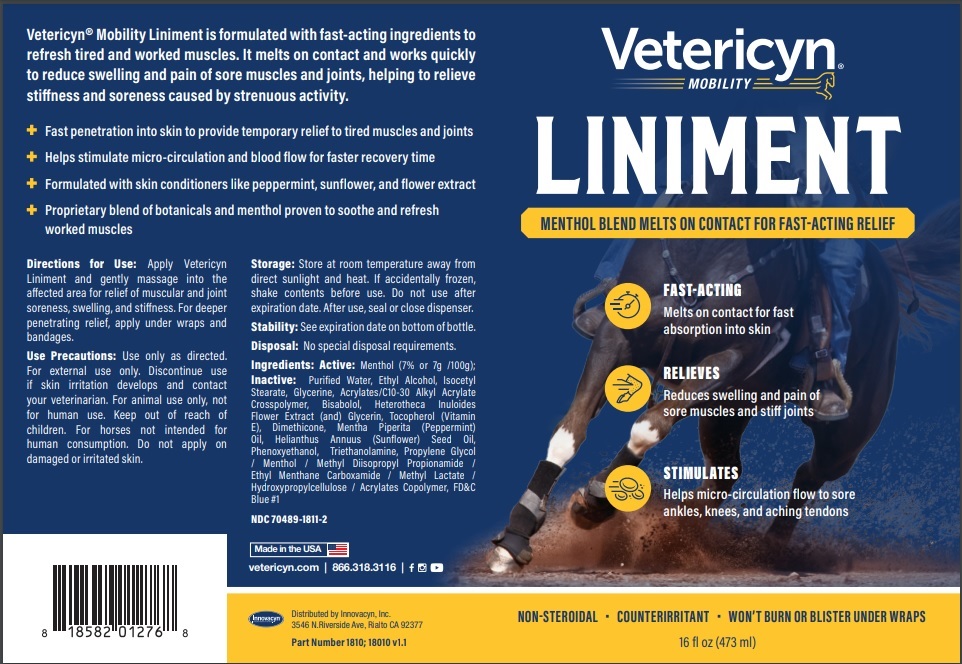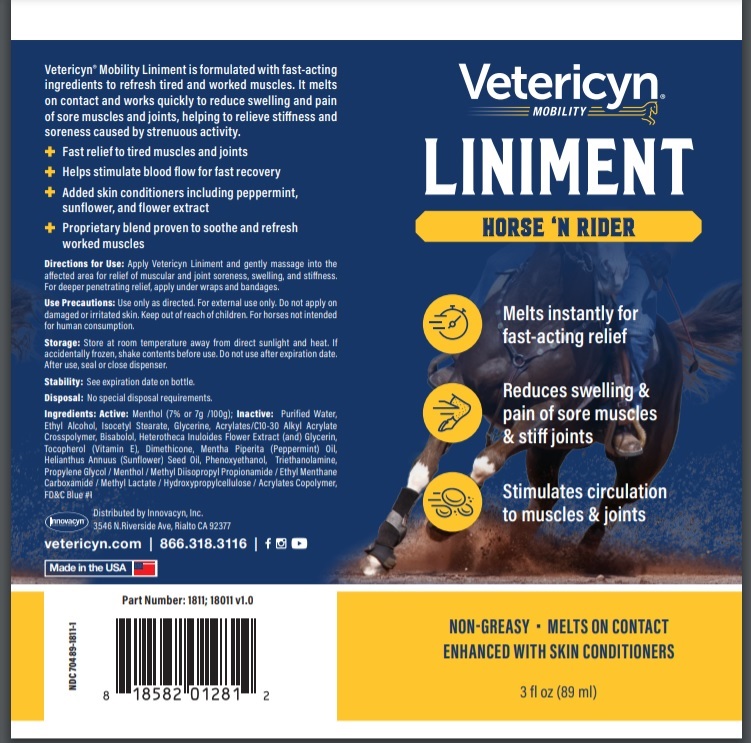 DRUG LABEL: Liniment
NDC: 70489-1811 | Form: GEL
Manufacturer: INNOVACYN INC.
Category: animal | Type: OTC ANIMAL DRUG LABEL
Date: 20251218

ACTIVE INGREDIENTS: MENTHOL 7 g/100 mL
INACTIVE INGREDIENTS: ALCOHOL; ISOCETYL STEARATE; GLYCERIN; CARBOMER INTERPOLYMER TYPE A (ALLYL SUCROSE CROSSLINKED); LEVOMENOL; HETEROTHECA INULOIDES FLOWER; TOCOPHEROL; DIMETHICONE; PEPPERMINT OIL; SUNFLOWER SEED; SUNFLOWER OIL; PHENOXYETHANOL; TROLAMINE; PROPYLENE GLYCOL; METHYL DIISOPROPYL PROPIONAMIDE; ETHYL MENTHANE CARBOXAMIDE; METHYL LACTATE, (-)-; HYDROXYPROPYL CELLULOSE, UNSPECIFIED; BUTYL ACRYLATE/METHYL METHACRYLATE/METHACRYLIC ACID COPOLYMER (18000 MW); FD&C BLUE NO. 1; WATER

LINIMENT

Active Ingredient

MENTHOL

Description

Vetericyn Mobility Liniment is formulated with fast-acting ingredients to

refresh tired and worked muscles. It melts on contact and works quickly

to reduce swelling and pain of sore muscles and joints, helping to relieve

stiffness and soreness caused by strenuous activity.

Dosage/Administration

Directions for Use: Apply Vetericyn Liniment and gently massage into the

affected area for relief of muscular and joint soreness, swelling, and stiffness. For deeper

penetrating relief, apply under wraps and bandages.

General Precautions

Use Precautions: Use only as directed.

For external use only.

Discontinue use if skin irritation develops and contact your veterinarian. For animal use only, not for human use.

Keep out of reach of children.

For horses not intended for human consumption.

Questions

vetericyn.com | 866.318.3116

Precautions

Storage: Store at room temperature away from direct sunlight and heat. If accidentally frozen,

shake contents before use. Do not use after expiration date. After use, seal or close dispenser.

Disposal: No special disposal requirements.

Stability: See expiration date on bottom of bottle.

Inactive Ingredient

Purified

Water, Ethyl Alcohol, Isocetyl Stearate, Glycerine,

Acrylates/C10-30 Alkyl Acrylate Crosspolymer,

Bisabolol, Heterotheca Inuloides Flower Extract

(and) Glycerin, Tocopherol (Vitamin E), Dimethicone,

Mentha Piperita (Peppermint) Oil, Helianthus Annuus

(Sunflower) Seed Oil, Phenoxyethanol, Triethanolamine,

Propylene Glycol / Menthol / Methyl Diisopropyl

Propionamide / Ethyl Menthane Carboxamide /

Methyl Lactate / Hydroxypropylcellulose / Acrylates,Copolymer, FD&C Blue #1